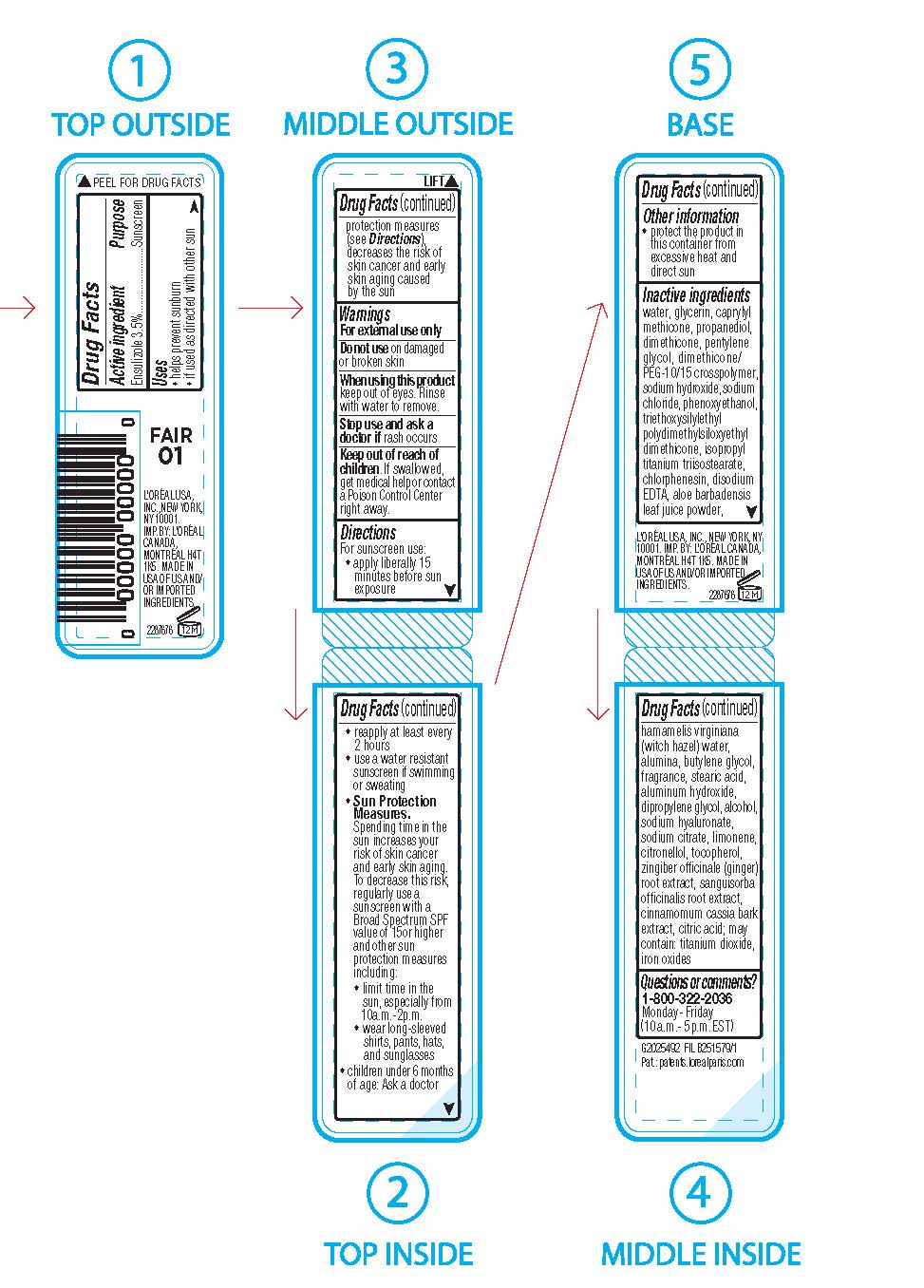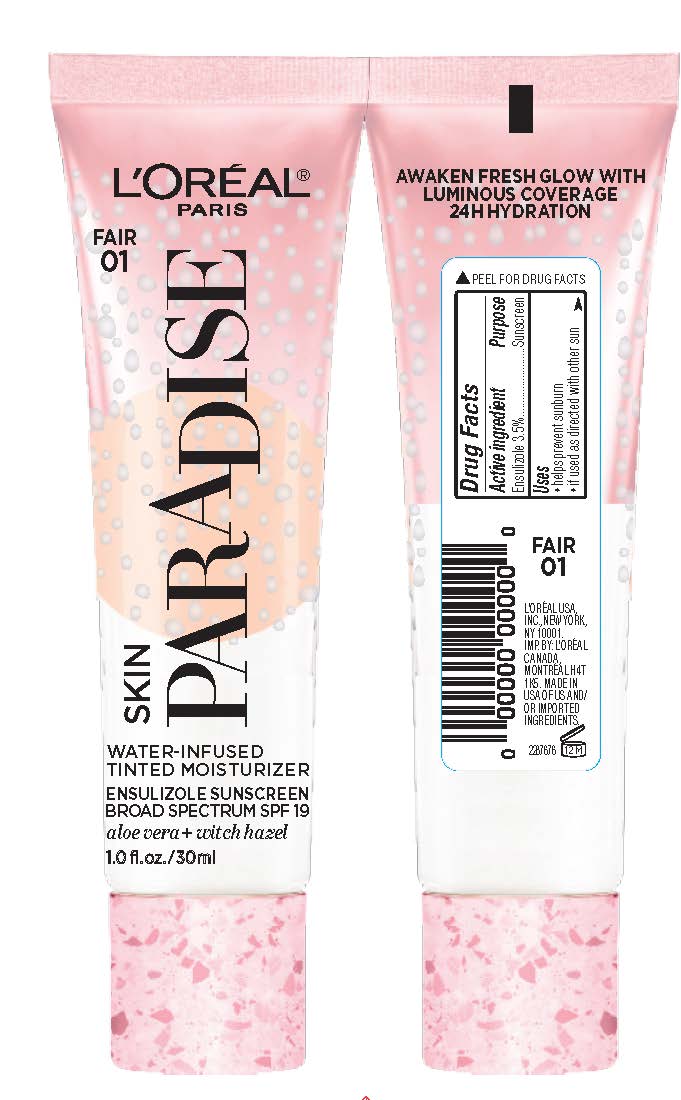 DRUG LABEL: LOreal Paris Skin Paradise Water Infused Tinted Moisturizer Broad Spectrum SPF 19 Sunscreen
NDC: 49967-767 | Form: LIQUID
Manufacturer: L'Oreal USA Products Inc
Category: otc | Type: HUMAN OTC DRUG LABEL
Date: 20240101

ACTIVE INGREDIENTS: ENSULIZOLE 35 mg/1 mL
INACTIVE INGREDIENTS: WATER; GLYCERIN; CAPRYLYL TRISILOXANE; PROPANEDIOL; DIMETHICONE; PENTYLENE GLYCOL; DIMETHICONE/PEG-10/15 CROSSPOLYMER; SODIUM HYDROXIDE; SODIUM CHLORIDE; PHENOXYETHANOL; ISOPROPYL TITANIUM TRIISOSTEARATE; CHLORPHENESIN; EDETATE DISODIUM ANHYDROUS; ALOE VERA LEAF; HAMAMELIS VIRGINIANA TOP WATER; ALUMINUM OXIDE; BUTYLENE GLYCOL; STEARIC ACID; ALUMINUM HYDROXIDE; DIPROPYLENE GLYCOL; ALCOHOL; HYALURONATE SODIUM; SODIUM CITRATE; LIMONENE, (+)-; .BETA.-CITRONELLOL, (R)-; TOCOPHEROL; GINGER; SANGUISORBA OFFICINALIS ROOT; CHINESE CINNAMON; CITRIC ACID MONOHYDRATE; TITANIUM DIOXIDE; FERRIC OXIDE RED

Drug Facts

Active ingredient

Ensulizole 3.5%

Purpose

Sunscreen

Uses

- helps prevent sunburn

- if used as directed with other sun protection measures (see Directions), decreases the risk of skin cancer and early skin aging caused by the sun

Warnings

For external use only

Do not use

on damaged or broken skin

When using this product

keep out of eyes. Rinse with water to remove.

Stop use and ask a doctor if

rash occurs

Keep out of reach of children.

If swallowed, get medical help or contact a Poison Control Center right away.

Directions

For sunscreen use:

● shake well before using

● apply liberally 15 minutes before sun exposure

● reapply at least every 2 hours

● use a water resistant sunscreen if swimming or sweating

● Sun Protection Measures. Spending time in the sun increases your risk of skin cancer and early skin aging. To decrease this risk, regularly use a sunscreen with a Broad Spectrum SPF value of 15 or higher and other sun protection measures including:

● limit time in the sun, especially from 10 a.m. – 2 p.m.

● wear long-sleeved shirts, pants, hats, and sunglasses

● children under 6 months of age: Ask a doctor

Other information

protect the product in this container from excessive heat and direct sun

Inactive ingredients

water, glycerin, caprylyl methicone, propanediol, dimethicone, pentylene glycol, dimethicone/PEG-10/15 crosspolymer, sodium hydroxide, sodium chloride, phenoxyethanol, triethoxysilylethyl polydimethylsiloxyethyl dimethicone, isopropyl titanium triisostearate, chlorphenesin, disodium EDTA, aloe barbadensis leaf juice powder, hamamelis virginiana (witch hazel) water, alumina, butylene glycol, fragrance,
stearic acid, aluminum hydroxide, dipropylene glycol, alcohol, sodium hyaluronate, sodium citrate, limonene, citronellol, tocopherol, zingiber officinale (ginger) root extract
sanguisorba officinalis root extract, cinnamomum cassia bark extract, citric acid; may contain: titanium dioxide, iron oxides

Questions or comments?

1-800-322-2036

Monday - Friday

(10 a.m. - 5 p.m. EST)